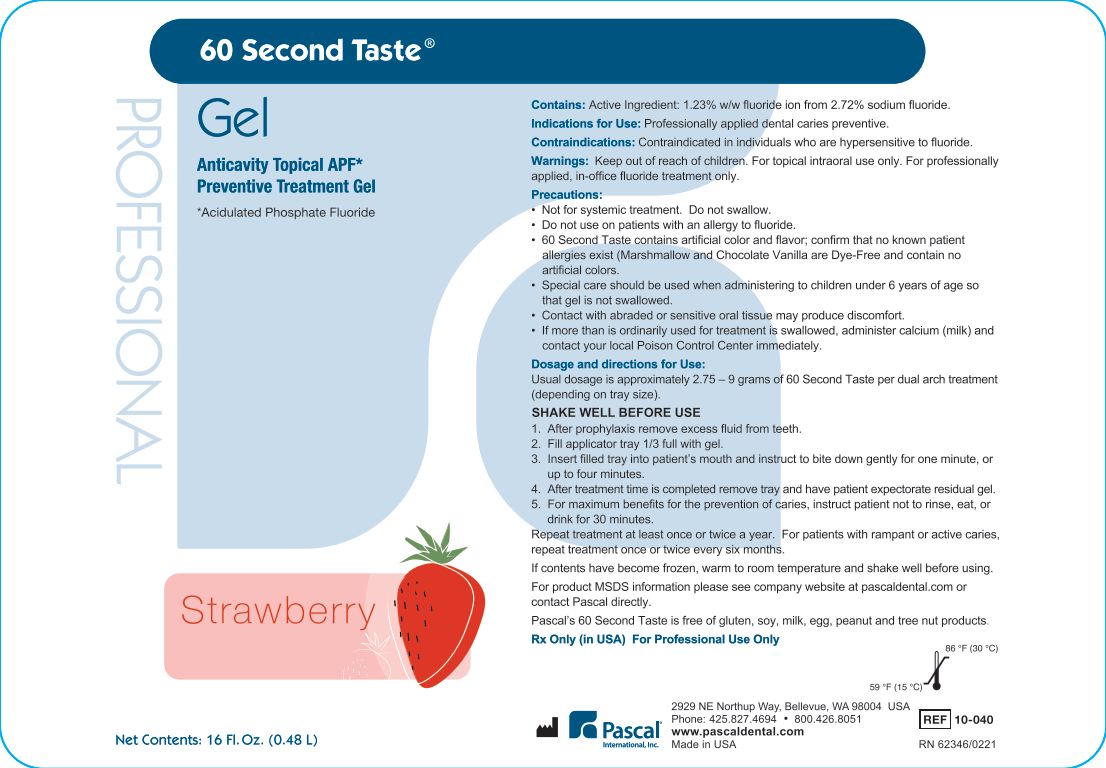 DRUG LABEL: 60 Second Taste Strawberry
NDC: 10866-0685 | Form: GEL
Manufacturer: Pascal Company, Inc.
Category: prescription | Type: HUMAN PRESCRIPTION DRUG LABEL
Date: 20251210

ACTIVE INGREDIENTS: Sodium Fluoride 27.73 mg/1 g

60 Second Taste Strawberry

Contains:

Active Ingredient: 1.23% w/w fluoride ion from 2.72% sodium fluoride

Contraindications:

Contraindicated in individuals who are hypersensitive to fluoride.

Warnings & Precautions

Keep out of reach of children. For topical intraoral use only. For Professionally applied in office fluoride treatment only.

Not for system treatment. Do not swallow.

Do not use on patients with an allergy to fluoride.

60 Second Taste contains artificial color and flavor; confirm that no known patient allergies exist. Marshmallow and Chocolate Vanilla are dye free and contain no artificial colors.

Special care should be used when administering to children under 6 years of age so that gel is not swallowed.

Contact with abraided or sensitive oral tissue may produce discomfort.

If more than is ordinarily used for treatment is swallowed, administer calcium such as milk and contact your local Poison Control Center immediately.

Dosage and directions for Use

Usual dosage is approximately 2.75 - 9 grams of 60 Second Taste per dual arch treatment (depending on tray size).

Shake well before use

1. After prophylaxis remove excess fluid from teeth.
2. Fill applicator tray 1/3 full with gel.
3. Insert filled tray into patient's mouth and instruct to bite down gently for one minute, or up to four minutes.
4. After treatment time is completed, remove tray and have patient expectorate residual gel.
5. For maximum benefits for the prevention of caries, instruct patient not to rinse, eat or drink for 30 minutes.

Repeat treatment at least once or twice a year. For patients with rampant or active caries, repeat treatment once or twice every six months.

If contents have become frozen, warm to room temperature and shake well before using.

Other Safety Information

For product MSDS information please see company website at pascaldental.com or contact Pascal directly.

Pascal's 60 Second Taste is free of gluten, soy, milk, egg, peanut and tree nut products.

Rx only in USA. For Professional Use Only.

PACKAGE LABEL

60 Second Taste Gel

Anticavity Topical APF*

Preventive Treatment Gel

*Acidulated Phosphate Fluoride

Strawberry